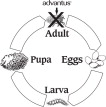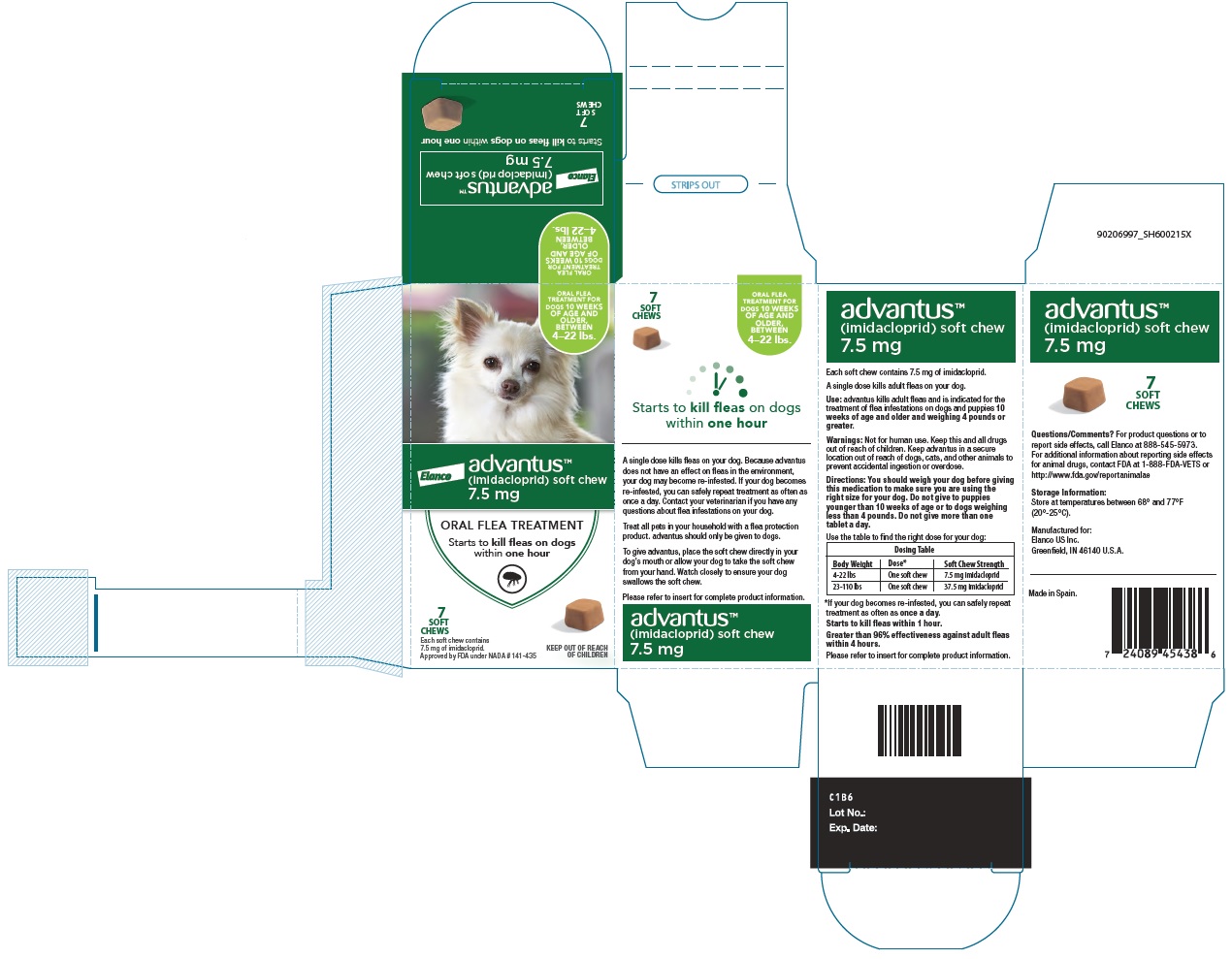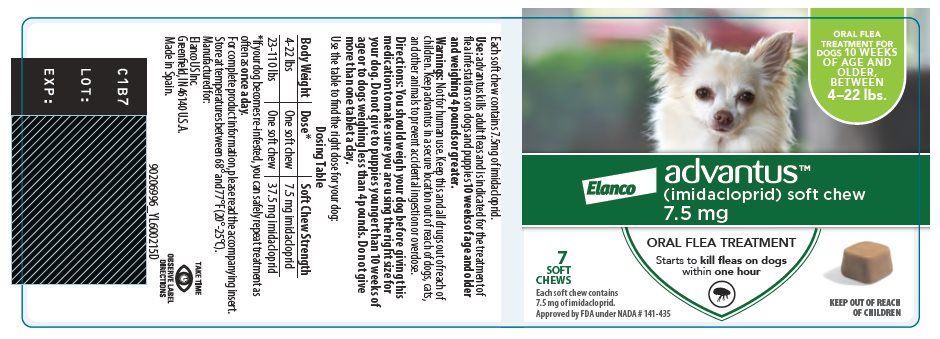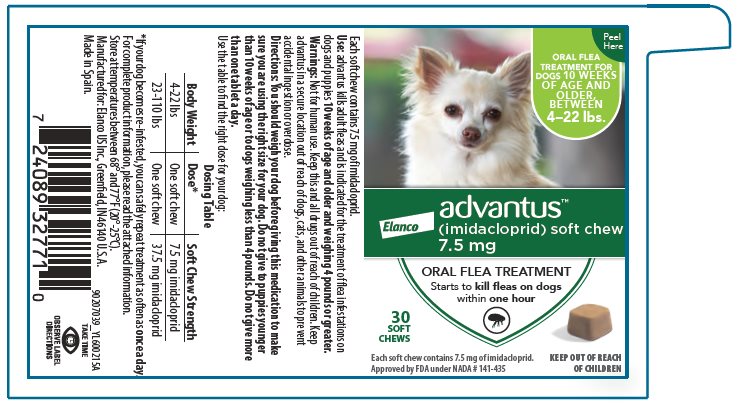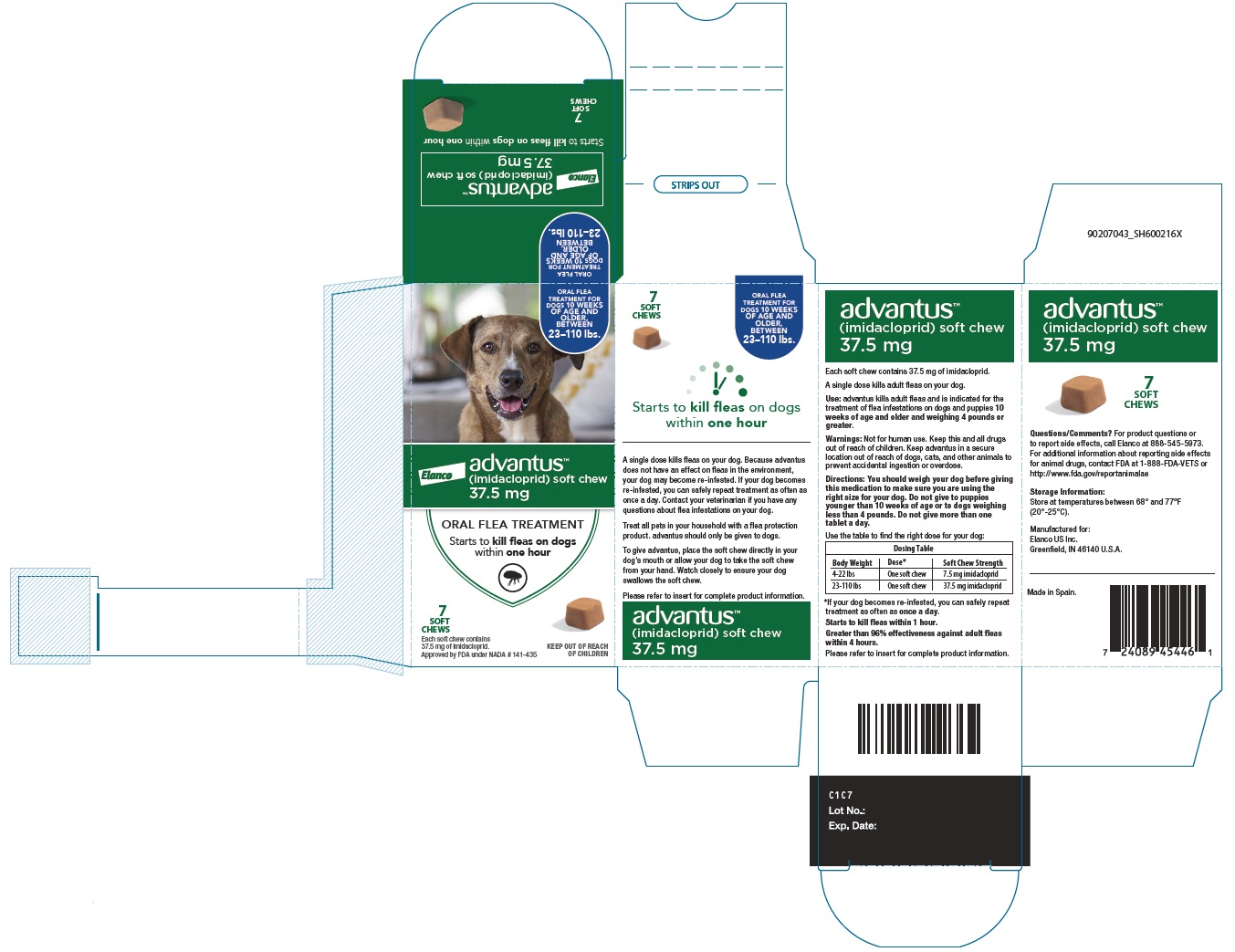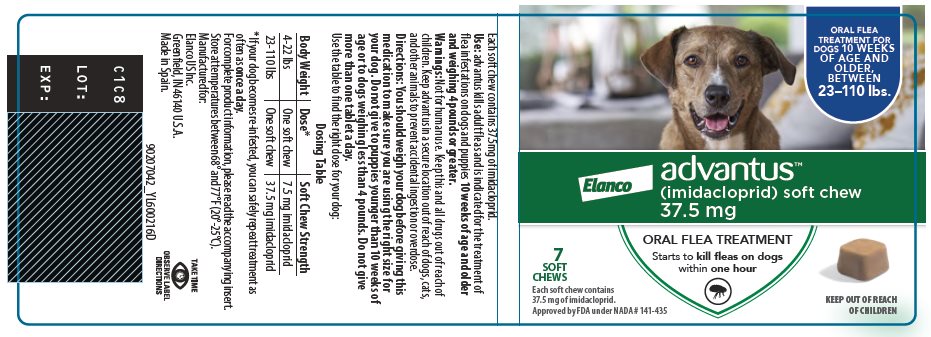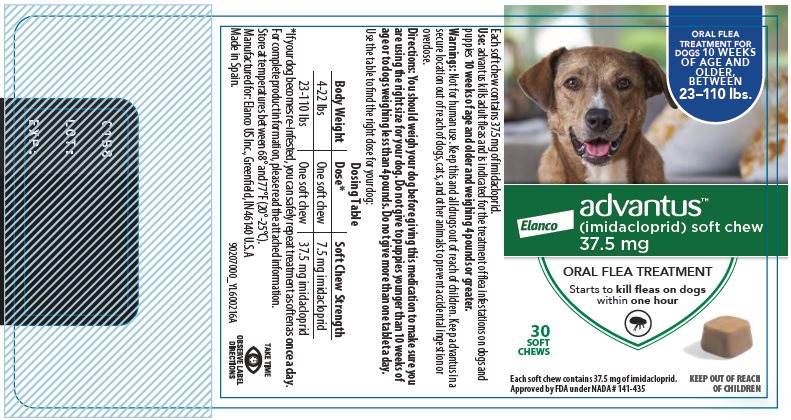 DRUG LABEL: Advantus
NDC: 58198-0017 | Form: TABLET, CHEWABLE
Manufacturer: Elanco US Inc.
Category: animal | Type: OTC ANIMAL DRUG LABEL
Date: 20250106

ACTIVE INGREDIENTS: IMIDACLOPRID 7.5 mg/1 1

advantusTM
(imidacloprid) soft chew

advantus is a flavored soft chew for dogs and puppies 10 weeks of age and older and weighing 4 pounds or greater.

Active Ingredients:

advantus contains 7.5 mg or 37.5 mg of imidacloprid.

Use:

advantus kills adult fleas and is indicated for the treatment of flea infestations on dogs and puppies 10 weeks of age and older and weighing 4 pounds or greater.

Warnings:

Not for human use. Keep this and all drugs out of reach of children.

Keep advantus in a secure location out of reach of dogs, cats, and other animals to prevent accidental ingestion or overdose.

Side Effects:

Side effects seen with this drug include vomiting, decreased appetite, decreased energy, soft stools and difficulty walking.

Directions:

You should weigh your dog before giving this medication to make sure you are using the right size for your dog. Do not give to puppies younger than 10 weeks of age or to dogs weighing less than 4 pounds. Do not give more than one tablet a day.

Use the table to find the right dose for your dog:

Dosing Table
Body Weight | Dose* | Soft Chew Strength
4-22 lbs | One Soft Chew | 7.5 mg imidacloprid
23-110 lbs | One Soft Chew | 37.5 mg imidacloprid
*If your dog becomes re-infested, you can safely repeat treatment as often as once a day.

To give advantus, place the soft chew directly in your dog's mouth or allow your dog to take the soft chew from your hand. Watch closely to ensure your dog swallows the soft chew.

A single dose kills adult fleas on your dog. Because advantus does not have an effect on fleas in the environment, your dog may become re-infested with fleas. If your dog becomes re-infested, you can safely repeat treatment as often as once a day. Contact your veterinarian if you have any questions about flea infestations on your dog.

Treat all pets in your household with a flea protection product. advantus should only be given to dogs.

Questions/Comments?

For product questions or to report side effects, call Elanco at 888-545-5973. For additional information about reporting side effects for animal drugs, contact FDA at 1-888-FDA-VETS or http://www.fda.gov/reportanimalae

Other Information:

- Contact your veterinarian if your dog ingests more than the recommended dose of advantus.
- advantus has not been tested in pregnant or nursing dogs.
- advantus starts to kill fleas within 1 hour. A study demonstrated that advantus achieves greater than 96% effectiveness against adult fleas within 4 hours.
- advantus may be used together with other products, including heartworm preventatives, corticosteroids, antibiotics, vaccines, de-worming medications and shampoos.
- advantus does not protect against ticks or mosquitoes.

Flea Infestations on Dogs:

Treatment of flea infestations is important to your dog's health. Fleas in your dog's environment can re-infest your dog. Therefore, you may need to treat with advantus more than one time. The following diagram illustrates the flea's life cycle and where advantus works:

Fleas reproduce rapidly. A single female flea may produce up to 2,000 eggs over her lifetime. Eggs hatch and may grow into adults in only three weeks. Adult female fleas feed by ingesting blood from your dog and lay eggs that drop off from your dog's coat. Within days, larvae hatch from these eggs and live undetected in your dog's surroundings, such as in the carpet and bedding. Fleas can emerge to re-infest your pet, continuing the life cycle. When these new fleas are seen on your dog, treat with advantus.

If you have any questions about flea treatment or medical problems associated with flea infestations, consult your veterinarian.

Storage Information:

Store at temperatures between 68° and 77°F (20°-25°C).

How Supplied:

advantus is available in two strengths: 7.5 mg or 37.5 mg imidacloprid. Both strengths are packaged in 7 count bottles containing 7 flavored soft chews or 30 count bottles containing 30 flavored soft chews.

Approved by FDA under NADA # 141-435

Manufactured for:
Elanco US Inc.
Greenfield, IN 46140 U.S.A.

90207038_PA600215X

Revised: January 2022

Made in Spain.

advantus, Elanco and the diagonal bar logo are trademarks of Elanco or its affiliates.

© 2022 Elanco or its affiliates

TAKE TIME

OBSERVE LABEL DIRECTIONS

ElancoTM

Principal Display Panel - 7.5 mg Carton Label

ORAL FLEA
TREATMENT FOR
DOGS 10 WEEKS
OF AGE AND
OLDER,
BETWEEN
4–22 lbs.

Elanco
advantusTM

(imidacloprid) soft chew

7.5 mg

ORAL FLEA TREATMENT

Starts to kill fleas on dogs
within one hour

7
SOFT
CHEWS

Each soft chew contains
7.5 mg of imidacloprid.

Approved by FDA under NADA # 141-435

KEEP OUT OF REACH
OF CHILDREN

Principal Display Panel - 7.5 mg 7 Soft Chews Bottle Label

ORAL FLEA
TREATMENT FOR
DOGS 10 WEEKS
OF AGE AND
OLDER,
BETWEEN
4–22 lbs.

Elanco
advantusTM

(imidacloprid) soft chew

7.5 mg

ORAL FLEA TREATMENT

Starts to kill fleas on dogs
within one hour

7
SOFT
CHEWS

Each soft chew contains
7.5 mg of imidacloprid.

Approved by FDA under NADA # 141-435

KEEP OUT OF REACH
OF CHILDREN

Principal Display Panel - 7.5 mg 30 Soft Chews Bottle Label

Peel
Here

ORAL FLEA
TREATMENT FOR
DOGS 10 WEEKS
OF AGE AND
OLDER,
BETWEEN
4–22 lbs.

Elanco
advantus™

(imidacloprid) soft chew

7.5 mg

ORAL FLEA TREATMENT

Starts to kill fleas on dogs
within one hour

30
SOFT
CHEWS

Each soft chew contains 7.5 mg of imidacloprid.

Approved by FDA under NADA # 141-435

KEEP OUT OF REACH
OF CHILDREN

Principal Display Panel - 37.5 mg Carton Label

ORAL FLEA
TREATMENT FOR
DOGS 10 WEEKS
OF AGE AND
OLDER,
BETWEEN
23–110 lbs.

Elanco
advantusTM

(imidacloprid) soft chew

37.5 mg

ORAL FLEA TREATMENT

Starts to kill fleas on dogs
within one hour

7
SOFT
CHEWS

Each soft chew contains
37.5 mg of imidacloprid.

Approved by FDA under NADA # 141-435

KEEP OUT OF REACH
OF CHILDREN

Principal Display Panel - 37.5 mg 7 Soft Chews Bottle Label

ORAL FLEA
TREATMENT FOR
DOGS 10 WEEKS
OF AGE AND
OLDER,
BETWEEN
23–110 lbs.

Elanco
advantusTM

(imidacloprid) soft chew

37.5 mg

ORAL FLEA TREATMENT

Starts to kill fleas on dogs
within one hour

7
SOFT
CHEWS

Each soft chew contains
37.5 mg of imidacloprid.

Approved by FDA under NADA # 141-435

KEEP OUT OF REACH
OF CHILDREN

Principal Display Panel - 37.5 mg 30 Soft Chews Bottle Label

Peel
Here

ORAL FLEA
TREATMENT FOR
DOGS 10 WEEKS
OF AGE AND
OLDER,
BETWEEN
23–110 lbs.

Elanco
advantus™

(imidacloprid) soft chew

37.5 mg

ORAL FLEA TREATMENT

Starts to kill fleas on dogs
within one hour

30
SOFT
CHEWS

Each soft chew contains 37.5 mg of imidacloprid.

Approved by FDA under NADA # 141-435

KEEP OUT OF REACH
OF CHILDREN